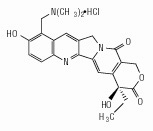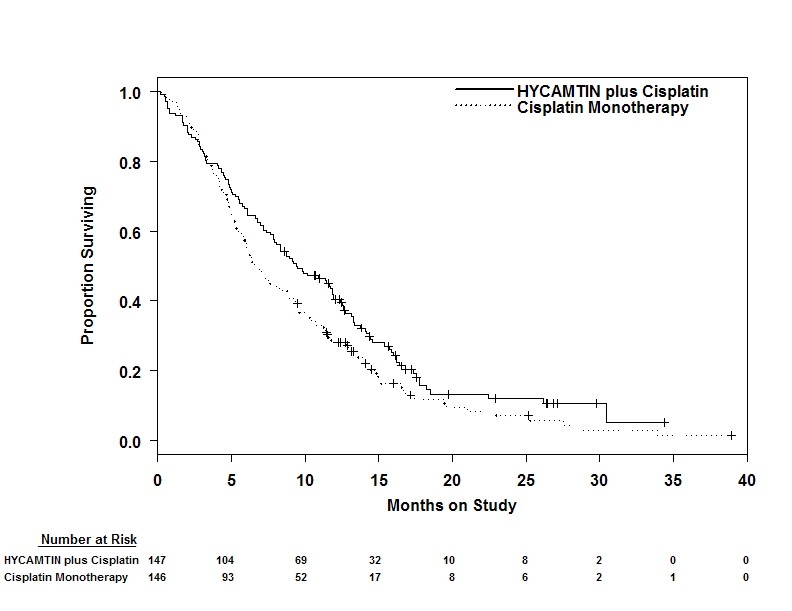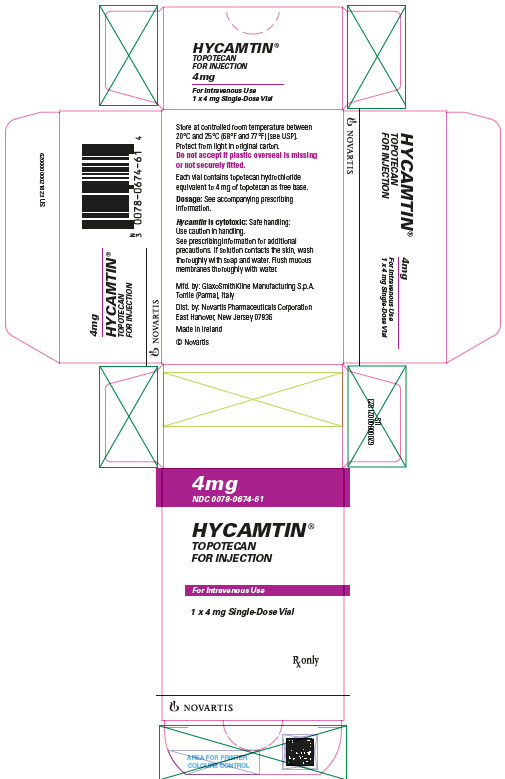 DRUG LABEL: HYCAMTIN
NDC: 0078-0674 | Form: INJECTION, POWDER, LYOPHILIZED, FOR SOLUTION
Manufacturer: Novartis Pharmaceuticals Corporation
Category: prescription | Type: HUMAN PRESCRIPTION DRUG LABEL
Date: 20220707

ACTIVE INGREDIENTS: TOPOTECAN HYDROCHLORIDE 4 mg/4 mL
INACTIVE INGREDIENTS: MANNITOL; TARTARIC ACID; HYDROCHLORIC ACID; SODIUM HYDROXIDE

HIGHLIGHTS OF PRESCRIBING INFORMATION

These highlights do not include all the information needed to use HYCAMTIN FOR INJECTION safely and effectively. See full prescribing information for HYCAMTIN FOR INJECTION.
HYCAMTIN® (topotecan) for injection, for intravenous use
Initial U.S. Approval: 1996

WARNING: MYELOSUPPRESSION

See full prescribing information for complete boxed warning.

HYCAMTIN can cause severe myelosuppression. Administer first cycle only to patients with baseline neutrophil counts greater than or equal to 1,500/mm^3 and platelet counts greater than or equal to 100,000/mm^3. Monitor blood cell counts (2.4, 5.1).

1 INDICATIONS AND USAGE

HYCAMTIN for injection is a topoisomerase inhibitor indicated for treatment of:

- Patients with metastatic ovarian cancer after disease progression on or after initial or subsequent chemotherapy, as a single agent (1.1)
- Patients with small cell lung cancer (SCLC) platinum-sensitive disease who progressed at least 60 days after initiation of first-line chemotherapy, as a single agent (1.2)
- Patients with Stage IV-B, recurrent, or persistent cervical cancer which is not amenable to curative treatment, in combination with cisplatin (1.3)

2 DOSAGE AND ADMINISTRATION

- Ovarian Cancer and Small Cell Lung Cancer: 1.5 mg/m^2 by intravenous infusion over 30 minutes daily for 5 consecutive days, starting on Day 1 of a 21-day cycle (2.2, 2.3)
- Cervical Cancer: 0.75 mg/m^2 by intravenous infusion over 30 minutes on Days 1, 2, and 3, with cisplatin 50 mg/m^2 on Day 1, of a 21-day cycle (2.4)
- Renal Impairment: Reduce dose if creatinine clearance (CLcr) 20 to 39 mL/min (2.6)

3 DOSAGE FORMS AND STRENGTHS

For injection: 4 mg (free base) lyophilized powder in single-dose vial (3)

4 CONTRAINDICATIONS

- History of severe hypersensitivity reactions to topotecan (4)

5 WARNINGS AND PRECAUTIONS

- Interstitial Lung Disease (ILD): Fatal cases have occurred. Permanently discontinue if ILD confirmed. (5.2)
- Extravasation and Tissue Injury: Severe cases have occurred. If extravasation occurs, immediately stop administration and institute recommended management procedures. (5.3)
- Embryo-Fetal Toxicity: Can cause fetal harm. Advise patients of potential risk to the fetus and to use effectives contraception. (5.4, 8.1, 8.3)

6 ADVERSE REACTIONS

Ovarian Cancer

- The most common Grade 3 or 4 hematologic adverse reactions (incidence > 5%) were neutropenia, anemia, thrombocytopenia, and febrile neutropenia. (6.1)
- The most common (incidence > 5%) non-hematologic adverse reactions (all Grades) were nausea, vomiting, fatigue, diarrhea, and dyspnea. (6.1)

SCLC

- The most common Grade 3 or 4 hematologic adverse reactions were (incidence > 5%) neutropenia, anemia, thrombocytopenia, and febrile neutropenia. (6.1)
- The most common (incidence > 5%) non-hematologic adverse reactions (all Grades) were asthenia, dyspnea, nausea, pneumonia, abdominal pain, and fatigue. (6.1)

Cervical Cancer

- The most common Grade 3 or 4 hematologic adverse reactions were (incidence > 5%) neutropenia, anemia, and thrombocytopenia. (6.1)
- The most common (incidence > 25% and ≥ 2% higher than cisplatin alone) non-hematologic adverse reactions were pain, vomiting, and infection/febrile neutropenia. (6.1)

To report SUSPECTED ADVERSE REACTIONS, contact Novartis Pharmaceuticals Corporation at 1-888-669-6682 or FDA at 1-800-FDA-1088 or www.fda.gov/medwatch.

8 USE IN SPECIFIC POPULATIONS

- Lactation: Advise not to breastfeed. (8.2)

FULL PRESCRIBING INFORMATION

WARNING: MYELOSUPPRESSION

HYCAMTIN can cause severe myelosuppression. Administer first cycle only to patients with baseline neutrophil counts of greater than or equal to 1,500/mm^3 and platelet counts greater than or equal to 100,000/mm^3. Monitor blood cell counts [see Warnings and Precautions (5.1)].

1 INDICATIONS AND USAGE

1.1 Ovarian Cancer

HYCAMTIN® for injection, as a single agent, is indicated for the treatment of patients with metastatic ovarian cancer after disease progression on or after initial or subsequent chemotherapy.

1.2 Small Cell Lung Cancer

HYCAMTIN for injection, as a single agent, is indicated for the treatment of patients with small cell lung cancer (SCLC) with platinum-sensitive disease who progressed at least 60 days after initiation of first‑line chemotherapy.

1.3 Cervical Cancer

HYCAMTIN for injection, in combination with cisplatin, is indicated for the treatment of patients with Stage IV-B, recurrent, or persistent cervical cancer not amenable to curative treatment.

2 DOSAGE AND ADMINISTRATION

2.1 Important Safety Information

Verify dosage using body surface area. Do not exceed a single dose of 4 mg intravenously.

2.2 Recommended Dosage for Ovarian Cancer

The recommended dosage of HYCAMTIN for injection is 1.5 mg/m^2 by intravenous infusion over 30 minutes daily for 5 consecutive days, starting on Day 1 of a 21-day cycle until disease progression or unacceptable toxicity.

2.3 Recommended Dosage for Small Cell Lung Cancer (SCLC)

The recommended dosage of HYCAMTIN for injection is 1.5 mg/m^2 by intravenous infusion over 30 minutes daily for 5 consecutive days, starting on Day 1 of a 21-day cycle.

2.4 Recommended Dosage for Cervical Cancer

The recommended dosage of HYCAMTIN for injection is 0.75 mg/m^2 by intravenous infusion over 30 minutes daily on Days 1, 2, and 3, in combination with cisplatin 50 mg/m^2 on Day 1, of a 21-day cycle.

2.5 Dosage Modifications for Adverse Reactions

Hematologic

Do not administer subsequent cycles of HYCAMTIN for injection until neutrophils recover to greater than 1,000/mm^3, platelets recover to greater than 100,000/mm^3, and hemoglobin levels recover to greater than or equal to 9 g/dL (with transfusion if necessary).

For HYCAMTIN for injection as a single agent, reduce the dose to 1.25 mg/m^2/day for:

- neutrophil counts of less than 500/mm^3 or administer granulocyte-colony stimulating factor (G-CSF) starting no sooner than 24 hours following the last dose
- platelet counts less than 25,000/mm^3 during previous cycle

For HYCAMTIN for injection in combination with cisplatin, reduce the dose to 0.6 mg/m^2/day (and further to 0.45 mg/m^2 if necessary) for:

- febrile neutropenia (defined as neutrophil counts less than 1,000/mm^3 with temperature of greater than or equal to 38.0°C (100.4°F) or administer G-CSF starting no sooner than 24 hours following the last dose
- platelet counts less than 25,000/mm^3 during previous cycle

2.6 Dosage Modification for Renal Impairment

For HYCAMTIN for injection as a single agent, reduce the dose to 0.75 mg/m^2/day for patients with creatinine clearance (CLcr) of 20 to 39 mL/min (calculated with the Cockcroft-Gault method using ideal body weight) [see Clinical Pharmacology (12.3)].

2.7 Preparation and Intravenous Administration

- Visually inspect for particulate matter and discoloration prior to administration, whenever solution and container permit.

Preparation

- Reconstitute each 4 mg vial of HYCAMTIN for injection with 4 mL Sterile Water for Injection, USP.
- Dilute the appropriate volume of the reconstituted solution in either 0.9% Sodium Chloride Intravenous Infusion, USP or 5% Dextrose in Water Injection, USP.

Stability

- Because the vials contain no preservative, use contents immediately after reconstitution. Discard any unused portion.
- Store reconstituted product diluted for infusion at approximately 20°C to 25°C (68°F to 77°F) protected from light for no more than 24 hours. Discard after 24 hours.

HYCAMTIN for injection is a cytotoxic drug. Follow applicable handling and disposal procedures.^1

3 DOSAGE FORMS AND STRENGTHS

For injection: 4 mg (free base) of topotecan as a light yellow to greenish lyophilized powder in single-dose vial for reconstitution.

4 CONTRAINDICATIONS

HYCAMTIN is contraindicated in patients who have a history of severe hypersensitivity reactions to topotecan. Reactions have included anaphylactoid reactions [see Adverse Reactions (6.2)].

5 WARNINGS AND PRECAUTIONS

5.1 Myelosuppression

HYCAMTIN can cause severe myelosuppression.

Single Agent

Grade 4 neutropenia occurred in 78% of 879 patients, with a median duration of 7 days and was most common during Cycle 1 (58% of patients). Grade 4 neutropenia associated with infection occurred in 13% and febrile neutropenia occurred in 5%. Sepsis occurred in 4% of patients and was fatal in 1%. Grade 4 thrombocytopenia occurred in 27%, with a median duration of 5 days. Grade 3 or 4 anemia occurred in 37% of patients.

Combination with Cisplatin

Grade 4 neutropenia occurred in 48% and Grade 4 thrombocytopenia occurred in 7% of 147 patients. Grade 3 or 4 anemia occurred in 40% of patients.

Topotecan can cause fatal typhlitis (neutropenic enterocolitis). Consider the possibility of typhlitis in patients presenting with fever, neutropenia, and abdominal pain.

Administer the first cycle of HYCAMTIN for injection only to patients with a baseline neutrophil count of greater than or equal to 1,500/mm^3 and a platelet count greater than or equal to 100,000/mm^3. Monitor blood counts frequently during treatment. Withhold and reduce dose of HYCAMTIN for injection based on neutrophil counts, platelet counts and hemoglobin levels [see Dosage and Administration (2.5)].

5.2 Interstitial Lung Disease

Interstitial lung disease (ILD), including fatalities, can occur with HYCAMTIN. Underlying risk factors include history of ILD, pulmonary fibrosis, lung cancer, thoracic radiation, and use of pneumotoxic drugs or colony stimulating factors. Monitor for pulmonary symptoms indicative of ILD. Permanently discontinue HYCAMTIN for injection if ILD is confirmed.

5.3 Extravasation and Tissue Injury

Extravasation, including severe cases, can occur with HYCAMTIN for injection. If signs or symptoms of extravasation occur, immediately stop administration of HYCAMTIN for injection and institute recommended management procedures [see Adverse Reactions (6.1)].

5.4 Embryo-Fetal Toxicity

Based on animal data, HYCAMTIN can cause fetal harm when administered to a pregnant woman. Topotecan caused embryolethality, fetotoxicity, and teratogenicity in rats and rabbits when administered during organogenesis. Advise women of the potential risk to a fetus. Advise females of reproductive potential to use effective contraception during treatment and for 6 months after the last dose of HYCAMTIN for injection. Advise males with a female partner of reproductive potential to use effective contraception during treatment with HYCAMTIN for injection and for 3 months after the last dose [see Use in Specific Populations (8.1, 8.3), Nonclinical Toxicology (13.1)].

6 ADVERSE REACTIONS

The following serious adverse reactions are described elsewhere in the labeling:

- Myelosuppression [see Warnings and Precautions (5.1)]
- Interstitial Lung Disease (ILD) [see Warnings and Precautions (5.2)]
- Extravasation and Tissue Injury [see Warnings and Precautions (5.3)]

6.1 Clinical Trials Experience

Because clinical trials are conducted under widely varying conditions, adverse reaction rates observed in the clinical trials of a drug cannot be directly compared with rates in the clinical trials of another drug and may not reflect the rates observed in practice.

The data in Warnings and Precautions reflect exposure to HYCAMTIN for injection from eight trials in which 879 patients with ovarian cancer or small cell lung cancer (SCLC) received HYCAMTIN for injection 1.5 mg/m^2 by intravenous infusion daily for 5 consecutive days, starting on Day 1 of a 21 day cycle and from one trial (Study GOG 0179) in which 147 patients with cervical cancer received HYCAMTIN for injection 0.75 mg/m^2 by intravenous infusion daily on Days 1, 2, and 3, with cisplatin 50 mg/m^2 by intravenous infusion on Day 1, of a 21-day cycle.

Ovarian Cancer

The safety of HYCAMTIN for injection was evaluated in a randomized trial conducted in 226 patients with metastatic ovarian cancer (Study 039) [see Clinical Studies (14.1)]. Table 1 shows the incidence of Grade 3 and 4 hematologic and non-hematologic adverse reactions that occurred in patients receiving HYCAMTIN for injection.

Table 1. Adverse Reactions Occurring in Greater than or Equal to 5% of Patients With Ovarian Cancer in Study 039
Adverse Reactions | HYCAMTIN for Injection; (n = 112) | Paclitaxel; (n = 114)
 | Grade 3-4 (%) | Grade 3-4 (%)
Hematologic
Grade 4 neutropenia (< 500/mm^3) Grade 3 or 4 anemia (Hgb < 8 g/dL) Grade 4 thrombocytopenia (< 25,000/mm^3) Febrile neutropenia | 80 41 27 23 | 21 6 3 4
Non-Hematologic
Infections
Sepsisa | 5 | 2
Respiratory, thoracic, and mediastinal
Dyspnea | 6 | 5
Gastrointestinal
Vomiting | 10 | 3
Nausea | 10 | 2
Diarrhea | 6 | 1
Abdominal pain | 5 | 4
Intestinal obstruction | 5 | 4
Constipation | 5 | 0
General and administrative site conditions
Fatigue | 7 | 6
Painb | 5 | 7
Asthenia | 5 | 3
aDeath related to sepsis occurred in 2% of patients receiving HYCAMTIN and 0% of patients receiving paclitaxel.
bPain includes body pain, skeletal pain, and back pain.

Small Cell Lung Cancer (SCLC)

The safety of HYCAMTIN for injection was evaluated in randomized, comparative trial in patients with recurrent or progressive SCLC (Study 090) [see Clinical Studies (14.2)]. Table 2 shows the Grade 3 or 4 hematologic and non-hematologic adverse reactions in patients with SCLC.

Table 2. Adverse Reactions Occurring in Greater than or Equal to 5% of Patients With Small Cell Lung Cancer in Study 090
Adverse Reactions | HYCAMTIN for Injection; (n = 107) | CAVc; (n = 104)
 | Grade 3-4 (%) | Grade 3-4 (%)
Hematologic
Grade 4 neutropenia (< 500/mm^3) Grade 3 or 4 anemia (Hgb < 8 g/dL) Grade 4 thrombocytopenia (< 25,000/mm^3) Febrile neutropenia | 70 42 29 28 | 72 20 5 26
Non-Hematologic
Infections
Sepsisa | 5 | 5
Respiratory, thoracic, and mediastinal
Dyspnea | 9 | 14
Pneumonia | 8 | 6
Gastrointestinal
Nausea | 8 | 6
Abdominal pain | 6 | 4
General and administrative site conditions
Asthenia | 9 | 7
Fatigue | 6 | 10
Painb | 5 | 7
aDeath related to sepsis occurred in 3% of patients receiving HYCAMTIN and 1% of patients receiving CAV.
bPain includes body pain, skeletal pain, and back pain.
cCAV = cyclophosphamide, doxorubicin and vincristine.

Hepatobiliary Disorders in Ovarian and Small Cell Lung Cancer (SCLC)

Based on the combined experience of 453 patients with metastatic ovarian cancer and 426 patients with SCLC treated with HYCAMTIN for injection, Grade 3 or 4 increases aspartate transaminase (AST) or alanine transaminase (ALT) occurred in 4% and Grade 3 or 4 elevated bilirubin occurred in less than 2%.

Cervical Cancer

The safety of HYCAMTIN for injection was evaluated in a comparative trial of HYCAMTIN with cisplatin versus cisplatin as a single agent in patients with cervical cancer (Study GOG 0179). Table 3 shows the hematologic and non-hematologic adverse reactions in patients with cervical cancer.

Table 3. Adverse Reactions Occurring in Greater than or Equal to 5% of Patients With Cervical Cancer (Between-Arm Difference ≥ 2%)a in Study GOG 0179
Adverse Reactions | HYCAMTIN for Injection With Cisplatin; (n = 140) % | Cisplatin; (n = 144) %
Hematologic
Neutropenia
Grade 3 (< 1,000-500/mm^3) | 26 | 1
Grade 4 (< 500/mm^3) | 48 | 1
Anemia
Grade 3 (Hgb < 8-6.5 g/dL) | 34 | 19
Grade 4 (Hgb < 6.5 g/dL) | 6 | 3
Thrombocytopenia
Grade 3 (< 50,000-10,000/mm^3) | 26 | 3
Grade 4 (< 10,000/mm^3) | 7 | 0
Non-Hematologicb,c
General and administrative site conditions
Constitutionald | 69 | 62
Paine | 59 | 50
Gastrointestinal
Vomiting | 40 | 37
Stomatitis-pharyngitis | 6 | 0
Other | 63 | 56
Dermatologyf | 48 | 20
Infection
Febrile neutropeniaf | 28 | 18
Cardiovascularf | 25 | 15
aIncludes patients who were eligible and treated.
bSeverity based on using National Cancer Institute (NCI) Common Toxicity Criteria (CTC), Version 2.0.
cGrades 1 through 4 only. There were 3 patients who experienced deaths with investigator-designated attribution. The first patient experienced a Grade 5 hemorrhage in which the drug-related thrombocytopenia aggravated the event. A second patient experienced bowel obstruction, cardiac arrest, pleural effusion, and respiratory failure which were not treatment-related but probably aggravated by treatment. A third patient experienced a pulmonary embolism and adult respiratory distress syndrome; the latter was indirectly treatment-related.
dConstitutional includes fatigue (lethargy, malaise, asthenia), fever (in the absence of neutropenia), rigors, chills, sweating, and weight gain or loss.
ePain includes abdominal pain or cramping, arthralgia, bone pain, chest pain (non-cardiac and non-pleuritic), dysmenorrhea, dyspareunia, earache, headache, hepatic pain, myalgia, neuropathic pain, pain due to radiation, pelvic pain, pleuritic pain, rectal or perirectal pain, and tumor pain.
fHigh-level terms were included if the between-arm difference was ≥ 10%.

6.2 Postmarketing Experience

The following reactions have been identified during post approval use of HYCAMTIN. Because these reactions are reported voluntarily from a population of unknown size, it is not always possible to reliably estimate their frequency or establish a causal relationship to drug exposure.

Blood and Lymphatic System: severe bleeding (in association with thrombocytopenia)

Hypersensitivity: allergic manifestations, anaphylactoid reactions, angioedema

Gastrointestinal: abdominal pain potentially associated with neutropenic enterocolitis, gastrointestinal perforation

Pulmonary: interstitial lung disease

Skin and Subcutaneous Tissue: severe dermatitis, severe pruritus

General and Administration Site Conditions: extravasation, mucosal inflammation

8 USE IN SPECIFIC POPULATIONS

8.1 Pregnancy

Risk Summary

Based on animal data and its mechanism of action, HYCAMTIN can cause fetal harm when administered to a pregnant woman. There are no available clinical data on the use of HYCAMTIN in pregnancy. Topotecan caused embryolethality, fetotoxicity, and teratogenicity in rats and rabbits when administered during organogenesis at doses similar to the clinical dose (see Data). Advise pregnant women of the potential risk to a fetus.

In the U.S. general population, the background risk of major birth defects is 2% to 4% and of miscarriage is 15% to 20% of clinically recognized pregnancies.

Data

Animal Data

In rabbits, an intravenous dose of 0.10 mg/kg/day [about equal to the 1.5 mg/m^2 clinical dose based on body surface area (BSA)] given on Days 6 through 20 of gestation caused maternal toxicity, embryolethality and reduced fetal body weight. In the rat, an intravenous dose of 0.23 mg/kg/day (about equal to the 1.5 mg/m^2 clinical dose based on BSA) given for 14 days before mating through gestation Day 6 caused fetal resorption, microphthalmia, pre-implant loss, and mild maternal toxicity. Administration of an intravenous dose of 0.10 mg/kg/day (about half the 1.5 mg/m^2 clinical dose based on BSA) given to rats on Days 6 through 17 of gestation caused an increase in post-implantation mortality. This dose also caused an increase in total fetal malformations. The most frequent malformations were of the eye (microphthalmia, anophthalmia, rosette formation of the retina, coloboma of the retina, ectopic orbit), brain (dilated lateral and third ventricles), skull, and vertebrae.

8.2 Lactation

Risk Summary

There are no data on the presence of topotecan or its metabolites in human milk or their effects on the breastfed infant or on milk production. Lactating rats excrete high concentrations of topotecan in milk (see Data). Because of the potential for serious adverse reactions in breastfed infants, advise women not to breastfeed during treatment with HYCAMTIN for injection and for 1 week after the last dose.

Data

Following intravenous administration of topotecan to lactating rats at a dose of 4.72 mg/m^2 (about twice the 1.5 mg/m^2 clinical dose based on BSA) to lactating rats, topotecan was excreted into milk at concentrations up to 48-fold higher than those in plasma.

8.3 Females and Males of Reproductive Potential

Pregnancy Testing

Verify pregnancy status of females of reproductive potential prior to initiating HYCAMTIN for injection [see Use in Specific Populations (8.1)].

Contraception

HYCAMTIN can cause fetal harm when administered to a pregnant woman [see Use in Specific Populations (8.1)].

Females

Advise females of reproductive potential to use effective contraception during treatment with HYCAMTIN for injection and for 6 months after the last dose.

Males

HYCAMTIN may damage spermatozoa, resulting in possible genetic and fetal abnormalities. Advise males with a female partner of reproductive potential to use effective contraception during treatment with HYCAMTIN for injection and for 3 months after the last dose [see Nonclinical Toxicology (13.1)].

Infertility

Females

HYCAMTIN can have both acute and long-term effects on fertility [see Nonclinical Toxicology (13.1)].

Males

Effects on spermatogenesis occurred in animals administered topotecan [see Nonclinical Toxicology (13.1)].

8.4 Pediatric Use

Safety and effectiveness in pediatric patients have not been established.

8.5 Geriatric Use

Of the 879 patients with metastatic ovarian cancer or small cell lung cancer in clinical trials of HYCAMTIN for injection, 32% were aged 65 years and older, while 3.8% were aged 75 years and older. Of the 140 patients with Stage IV-B, relapsed, or refractory cervical cancer in clinical trials of HYCAMTIN for injection who received HYCAMTIN with cisplatin in the randomized clinical trial, 6% were aged 65 years and older, while 3% were aged 75 years and older. No overall differences in effectiveness or safety were observed between these patients and younger patients and other reported clinical experience has not identified differences in responses between the elderly and younger patients.

8.6 Renal Impairment

Reduce the dose of HYCAMTIN for injection in patients with a CLcr of 20 to 39 mL/min [see Dosage and Administration (2.6), Clinical Pharmacology (12.3)]. No dosage adjustment is recommended for patients with CLcr greater than or equal to 40 mL/min. Insufficient data are available in patients with CLcr less than 20 mL/min to provide a dosage recommendation for HYCAMTIN for injection.

10 OVERDOSAGE

Overdoses (up to 10-fold of the recommended dose) have occurred in patients receiving intravenous topotecan. The primary complication of overdosage is myelosuppression. Elevated hepatic enzymes, mucositis, gastrointestinal toxicity, and skin toxicity have occurred with overdosages. If an overdose is suspected, monitor the patient closely for myelosuppression and institute supportive-care measures as appropriate.

11 DESCRIPTION

Topotecan is a topoisomerase inhibitor. The chemical name for topotecan hydrochloride is (S)-10-[(dimethylamino)methyl]-4-ethyl-4,9-dihydroxy-1H-pyrano[3’,4’:6,7] indolizino [1,2-b]quinoline-3,14-(4H,12H)-dione monohydrochloride. The molecular formula is C23H23N3O5•HCl and the molecular weight is 457.9 g/mol. It is soluble in water and melts with decomposition at 213ºC to 218ºC.

Topotecan hydrochloride has the following structural formula:

HYCAMTIN (topotecan) for injection, for intravenous use is supplied as a sterile, lyophilized, buffered, light yellow to greenish powder available in single-dose vials. Each 4 mg vial contains 4 mg topotecan hydrochloride as free base. The reconstituted solution ranges in color from yellow to yellow-green.

Inactive ingredients are mannitol, 48 mg, and tartaric acid, 20 mg. Hydrochloric acid and sodium hydroxide may be used to adjust the pH. The solution pH ranges from 2.5 to 3.5.

12 CLINICAL PHARMACOLOGY

12.1 Mechanism of Action

Topoisomerase I relieves torsional strain in DNA by inducing reversible single-strand breaks. Topotecan binds to the topoisomerase I‑DNA complex and prevents re-ligation of these single-strand breaks. The cytotoxicity of topotecan is thought to be due to double-strand DNA damage produced during DNA synthesis, when replication enzymes interact with the ternary complex formed by topotecan, topoisomerase I, and DNA. Mammalian cells cannot efficiently repair these double-strand breaks.

12.3 Pharmacokinetics

Following administration of HYCAMTIN for injection at doses of 0.5 to 1.5 mg/m^2 (0.1 to 0.3 times the recommended single agent dose) administered as a 30-minute infusion, area under the curve (AUC) increases proportionally with dose.

Distribution

Protein binding of topotecan is approximately 35%.

Elimination

The terminal half-life of topotecan is 2 to 3 hours following intravenous administration.

Metabolism

Topotecan undergoes a reversible pH-dependent hydrolysis of its pharmacologically active lactone moiety. At pH less than or equal to 4, the lactone is exclusively present, whereas the ring-opened hydroxy-acid form predominates at physiologic pH. Topotecan is metabolized to an N-demethylated metabolite in vitro. The mean metabolite: parent AUC ratio was about 3% for total topotecan and topotecan lactone following intravenous administration.

Excretion

The overall recovery of total topotecan and its N-desmethyl metabolite in urine and feces over 9 days averaged 73% ± 2% following an intravenous dose. Mean values of 51% ± 3% as total topotecan and 3% ± 1% as N-desmethyl topotecan were excreted in the urine. Fecal elimination of total topotecan accounted for 18% ± 4% while fecal elimination of N-desmethyl topotecan was 1.7% ± 0.6%. An O-glucuronidation metabolite of topotecan and N-desmethyl topotecan has been identified in the urine.

Specific Populations

No clinically significant differences in the pharmacokinetics of topotecan were observed based on age, sex, or hepatic impairment following intravenous administration.

Patients with Renal Impairment

Compared to patients with CLcr (calculated by the Cockcroft-Gault method using ideal body weight) greater than 60 mL/min, plasma clearance of topotecan lactone decreased by 33% in patients with CLcr 40-60 mL/min and decreased 65% in patients with CLcr 20-39 mL/min. The effect on topotecan pharmacokinetics in patients with CLcr less than 20 mL/min is unknown [see Dosage and Administration (2.6)].

Drug Interaction Studies

Clinical Studies

No clinically significant changes in topotecan pharmacokinetics were observed when coadministered cisplatin.

No clinically significant changes in the pharmacokinetics of free platinum were observed in patients coadministered cisplatin with topotecan.

In Vitro Studies

Topotecan does not inhibit CYP1A2, CYP2A6, CYP2C8/9, CYP2C19, CYP2D6, CYP2E, CYP3A, or CYP4A or dihydropyrimidine dehydrogenase.

13 NONCLINICAL TOXICOLOGY

13.1 Carcinogenesis, Mutagenesis, Impairment of Fertility

Carcinogenicity testing of topotecan has not been performed. Topotecan is known to be genotoxic to mammalian cells and is a probable carcinogen. Topotecan was mutagenic to L5178Y mouse lymphoma cells and clastogenic to cultured human lymphocytes with and without metabolic activation. It was also clastogenic to mouse bone marrow. Topotecan did not cause mutations in bacterial cells.

Topotecan given to female rats prior to mating at an intravenous dose of 1.4 mg/m^2 [about equal to the clinical dose based on body surface area (BSA)] caused superovulation possibly related to inhibition of follicular atresia. This dose given to pregnant female rats also caused increased pre-implantation loss. Studies in dogs given at an intravenous dose of 0.4 mg/m^2 (about 0.25 times the clinical dose based on BSA) of topotecan daily for a month suggest that treatment may cause an increase in the incidence of multinucleated spermatogonial giant cells in the testes.

14 CLINICAL STUDIES

14.1 Ovarian Cancer

The efficacy of HYCAMTIN for injection was evaluated in two clinical trials of 223 patients with metastatic ovarian cancer. All patients had disease that had recurred on, or was unresponsive to, a platinum-containing regimen. Patients in these trials received an initial dose of 1.5 mg/m^2 as an intravenous infusion for 5 consecutive days, starting on Day 1 of a 21-day cycle.

One trial (Study 039) was a randomized trial of 112 patients who received HYCAMTIN for injection and of 114 patients who received paclitaxel (175 mg/m^2 intravenously over 3 hours on Day 1 of a 21-day cycle). All patients had recurrent ovarian cancer after a platinum-containing regimen or had not responded to at least 1 prior platinum-containing regimen. Patients who did not respond to the trial therapy, or who progressed, could be given the alternative treatment. The efficacy outcome measures were overall response rate, response duration, time to progression, and overall survival (OS).

The results of the trial did not show statistically significant improvements in response rates, response duration, time to progression, and OS as shown in Table 4.

Table 4. Efficacy Results in Ovarian Cancer in Study 039
Parameters | HYCAMTIN for Injection; (n = 112) | Paclitaxel; (n = 114)
Overall response rate (95% CI) | 21% (13%, 28%) | 14% (8%, 20%)
Complete response rate | 5% | 3%
Partial response rate | 16% | 11%
Response durationa (months)
Median (95% CI) | 6 (5.1, 7.6) | 5 (3.7, 7.8)
Time to progression (months)
Median (95% CI) | 4.4 (2.8, 5.4) | 3.4 (2.7, 4.2)
Hazard ratio (95% CI) | 0.76 (0.57, 1.02)
Overall survival (months)
Median (95% CI) | 14.5 (10.7, 16.5) | 12.2 (9.7, 15.8)
Hazard ratio (95% CI) | 0.97 (0.71, 1.34)
Abbreviation: CI, confidence interval.
aThe calculation for response duration was based on the interval between first response and time to progression.

The median time to response was 7.6 weeks (3.1 weeks to 5 months) with HYCAMTIN for injection compared with 6 weeks (2.4 weeks to 4.1 months) with paclitaxel. In the cross-over phase, 13% of 61 patients who received HYCAMTIN after paclitaxel had a partial response and 10% of 49 patients who received paclitaxel after HYCAMTIN had a response (2 complete responses).

HYCAMTIN for injection was active in ovarian cancer patients who had developed resistance to platinum-containing therapy, defined as tumor progression while on, or tumor relapse within 6 months after completion of, a platinum-containing regimen. One complete and 6 partial responses were seen in 60 patients, for a response rate of 12%. In the same trial, there were no complete responders and 4 partial responders on the paclitaxel arm, for a response rate of 7%.

HYCAMTIN for injection was also studied in an open-label, non-comparative trial in 111 patients with recurrent ovarian cancer after treatment with a platinum-containing regimen, or who had not responded to 1 prior platinum-containing regimen. The response rate was 14% (95% CI: 7%, 20%). The median duration of response was 5 months (4.6 weeks to 9.6 months). The time to progression was 2.6 months (5 days to 1.4 years). The median survival was 1.3 years (1.4 weeks, to 2.2 years).

14.2 Small Cell Lung Cancer (SCLC)

The efficacy of HYCAMTIN for injection was evaluated in 426 patients with recurrent or progressive small cell lung cancer (SCLC) in a randomized, comparative trial and in 3 single-arm trials.

Randomized Comparative Trial

In a randomized, comparative trial, 211 patients were randomized 1:1 to receive HYCAMTIN for injection (1.5 mg/m^2 once daily intravenously for 5 days starting on Day 1 of a 21-day cycle) or CAV (cyclophosphamide 1,000 mg/m^2, doxorubicin 45 mg/m^2, vincristine 2 mg administered sequentially on Day 1 of a 21-day cycle). All patients were considered sensitive to first-line chemotherapy (responders who then subsequently progressed greater than or equal to 60 days after completion of first-line therapy). A total of 77% of patients treated with HYCAMTIN for injection and 79% of patients treated with CAV received platinum/etoposide with or without other agents as first-line chemotherapy. The efficacy outcome measures were overall response rate, response duration, time to progression or OS.

The results of the trial did not show statistically significant improvements in response rate, response duration, time to progression, or OS as shown in Table 5.

Table 5. Efficacy Results in Patients With Small Cell Lung Cancer Sensitive to First-Line Chemotherapy in Study 090
Parameter | HYCAMTIN for Injection; (n = 107) | CAVb; (n = 104)
Overall response rate (95% CI) | 24% (16%, 32%) | 18% (11%, 26%)
Complete response rate | 0% | 1%
Partial response rate | 24% | 17%
Response durationa (months)
Median (95% CI) | 3.3 (3, 4.1) | 3.5 (3, 5.3)
Time to progression (months)
Median (95% CI) | 3.1 (2.6, 4.1) | 2.8 (2.5, 3.2)
Hazard ratio (95% CI) | 0.92 (0.69, 1.22)
Overall survival (months)
Median (95% CI) | 5.8 (4.7, 6.8) | 5.7 (5, 7)
Hazard ratio (95% CI) | 1.04 (0.78, 1.39)
Abbreviations: CI, confidence interval.
aThe calculation for duration of response was based on the interval between first response and time to progression.
bCAV = cyclophosphamide, doxorubicin and vincristine.

The median time to response was similar in both arms: HYCAMTIN, 6 weeks (2.4 weeks to 3.6 months) versus CAV, 6 weeks (5.1 weeks to 4.2 months).

Changes on a disease-related symptom scale are presented in Table 6. It should be noted that not all patients had all symptoms, nor did all patients respond to all questions. Each symptom was rated on a 4-category scale with an improvement defined as a change in 1 category from baseline sustained over 2 courses. Limitations in interpretation of the rating scale and responses preclude formal statistical analysis.

Table 6. Symptom Improvementa in Patients With Small Cell Lung Cancer in Study 090
Symptoms | HYCAMTIN for Injection; (n = 107) |  | CAV; (n = 104)
Symptoms | nb | (%) | nb | (%)
Shortness of breath | 68 | 28 | 61 | 7
Interference with daily activity | 67 | 27 | 63 | 11
Fatigue | 70 | 23 | 65 | 9
Hoarseness | 40 | 33 | 38 | 13
Cough | 69 | 25 | 61 | 15
Insomnia | 57 | 33 | 53 | 19
Anorexia | 56 | 32 | 57 | 16
Chest pain | 44 | 25 | 41 | 17
Hemoptysis | 15 | 27 | 12 | 33
aDefined as improvement sustained over at least 2 courses compared with baseline.
bNumber of patients with baseline and at least 1 post-baseline assessment.

Single-Arm Trials

HYCAMTIN for injection was also studied in three open-label, non-comparative trials (Studies 014, 092 and 053) in a total of 319 patients with recurrent or progressive SCLC after treatment with first-line chemotherapy. In all three trials, patients were stratified as either sensitive (responders who then subsequently progressed greater than or equal to 90 days after completion of first-line therapy) or refractory (no response to first-line chemotherapy or who responded to first-line therapy and then progressed within 90 days of completing first-line therapy). Response rates ranged from 11% to 31% for sensitive patients and 2% to 7% for refractory patients. Median time to progression and median survival were similar in all three trials and the comparative trial.

14.3 Cervical Cancer

The efficacy of HYCAMTIN for injection was evaluated in a multi-center, randomized (1:1), open-label study (Study GOG 0179) conducted in 147 patients with histologically confirmed Stage IV-B, recurrent, or persistent cervical cancer considered not amenable to curative treatment with surgery and/or radiation. Patients were randomized to HYCAMTIN for injection (0.75 mg/m^2 once daily intravenously for 3 consecutive days starting on Day 1 of a 21-day cycle) with cisplatin (50 mg/m^2 intravenously on Day 1) or cisplatin as a single agent. Fifty-six percent of patients treated with HYCAMTIN with cisplatin and 56% of patients treated with cisplatin had received prior cisplatin with or without other agents as first-line chemotherapy. The efficacy outcome measure was OS.

Median OS of eligible patients receiving HYCAMTIN with cisplatin was 9.4 months (95% CI: 7.9, 11.9) compared with 6.5 months (95% CI: 5.8, 8.8) among patients randomized to cisplatin alone with a log rank P-value of 0.033 (significance level was 0.044 after adjusting for the interim analysis). The unadjusted hazard ratio for OS was 0.76 (95% CI: 0.59, 0.98).

Figure 1. Kaplan-Meier Curves for Overall Survival in Cervical Cancer in Study GOG 0179

15 REFERENCES

1. "OSHA Hazardous Drugs." OSHA. http://www.osha.gov/SLTC/hazardousdrugs/index.html.

16 HOW SUPPLIED/STORAGE AND HANDLING

HYCAMTIN for injection is supplied as a sterile, lyophilized, buffered, light yellow to greenish powder for reconstitution in 4-mg (free base) single-dose vials.

NDC 0078-0674-61 (package of 1)

Store between 20°C and 25°C (68°F and 77°F) [see USP Controlled Room Temperature] in original carton. Protect from light.

HYCAMTIN for injection is a cytotoxic drug. Follow applicable handling and disposal procedures.^1

17 PATIENT COUNSELING INFORMATION

Myelosuppression

Inform patients that HYCAMTIN decreases blood cell counts such as white blood cells, platelets, and red blood cells. Advise patients to notify their healthcare provider promptly for fever, other signs of infection, or bleeding [see Warnings and Precautions (5.1)].

Interstitial Lung Disease (ILD)

Inform patients of the risks of severe ILD. Advise patients to contact their healthcare provider immediately to report new or worsening respiratory symptoms [see Warnings and Precautions (5.2)].

Embryo-Fetal Toxicity

Advise females of reproductive potential and males with female partners of reproductive potential of the potential risk to a fetus. Advise women to contact their healthcare provider if they become pregnant, or if pregnancy is suspected during treatment with HYCAMTIN for injection [see Warnings and Precautions (5.4), Use in Specific Populations (8.1, 8.3)].

Advise females of reproductive potential to use effective contraception during treatment and for 6 months after the last dose of HYCAMTIN for injection [see Use in Specific Populations (8.1, 8.3)].

Advise males with a female partner of reproductive potential to use effective contraception during treatment and for 3 months after the last dose of HYCAMTIN for injection [see Use in Specific Populations (8.1, 8.3), Nonclinical Toxicology (13.1)].

Lactation

Advise women to discontinue breastfeeding during treatment and for 1 week after the last dose of HYCAMTIN for injection [see Use in Specific Populations (8.2)].

Infertility

Advise male and female patients of the potential risk for impaired fertility [see Use in Specific Populations (8.3), Nonclinical Toxicology (13.1)].

Asthenia and Fatigue

Advise patients that HYCAMTIN for injection may cause asthenia or fatigue. These symptoms may impair the ability to safely drive or operate machinery.

Distributed by:
Novartis Pharmaceuticals Corporation
East Hanover, New Jersey 07936

© Novartis

T2019-115

PACKAGE LABEL

PRINCIPAL DISPLAY PANEL

NDC 0078-0674-61

4 mg

HYCAMTIN®

TOPOTECAN

FOR INJECTION

For Intravenous Use

1 x 4 mg Single-Dose Vial

Rx only

NOVARTIS